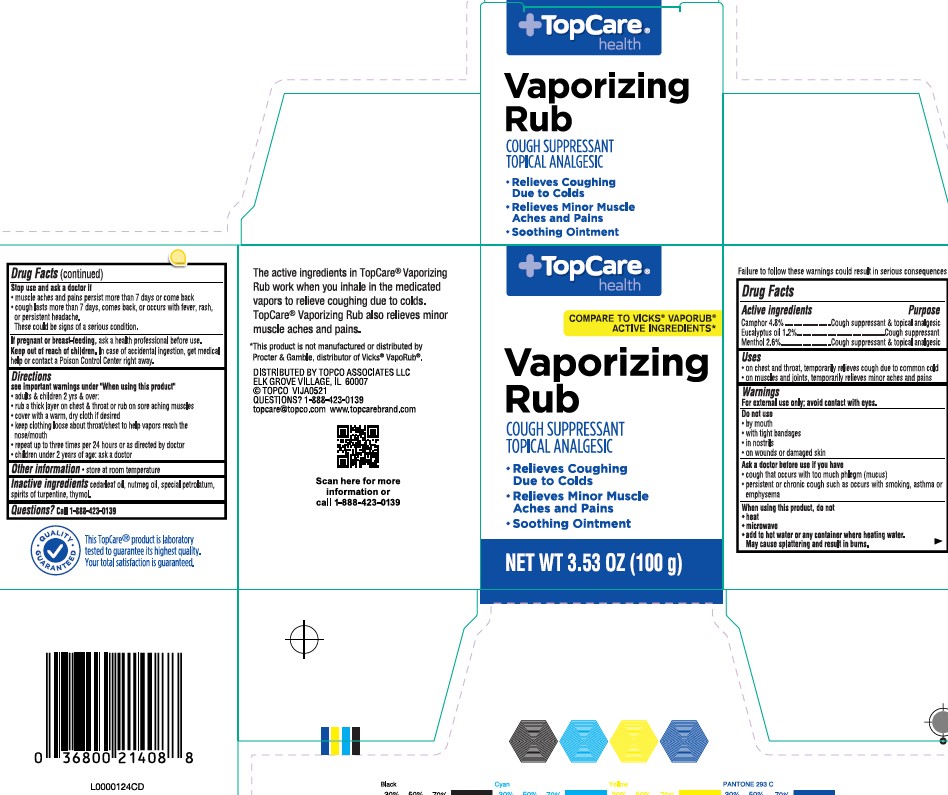 DRUG LABEL: Chest Rub
NDC: 36800-596 | Form: JELLY
Manufacturer: Topco Associates LLC
Category: otc | Type: HUMAN OTC DRUG LABEL
Date: 20260213

ACTIVE INGREDIENTS: CAMPHOR (SYNTHETIC) 48 mg/1 g; EUCALYPTUS OIL 12 mg/1 g; MENTHOL 26 mg/1 g
INACTIVE INGREDIENTS: NUTMEG OIL; CEDAR LEAF OIL; PETROLATUM; TURPENTINE OIL; THYMOL

Top Care 248.001/248AI
Medicated Chest Rub

Additional warnings

Failure to follow these warnings could result in serious consequences

Active ingredients

Camphor 4.8%

Eucalyptus oil 1.2%

Menthol 2.6%

Purpose

Cough suppressant & topical analgesic

Uses

- on chest and throat, temporarily relieves cough due to the common cold
- on muscles and joints, temporarily relieves minor aches and pains

Warnings

For external use only; avoid contact with eyes.

Do not use

- by mouth
- with tight bandages
- in nostrils
- on wounds or damaged skin

Ask a doctor before use if you have

- cough that occurs with too much phlegm (mucus)
- persistent or chronic cough such as occurs with smoking, asthma or emphysema

When using this product, do not

- heat
- microwave
- add to hot water or any container where heating water.
  May cause splattering and result in burns.

Stop use and ask a doctor if

- muscle aches and pains persist more than 7 days or come back
- cough lasts more than 7 days, comes back, or occurs with fever, rash or persistent headache.

This could be signs of a serious condition.

If pregnant or breast-feeding,

ask a health professional before use.

Keep out of reach of children

In case of accidental ingestion, get medical help or contact a Poison Control Center right away.

Directions

See important warnings under "When using this product"

- adults & children 2 yrs & over:
- rub a thick layer on chest & throat or rub on sore aching muscles
- cover with a warm, dry cloth if desired
- keep clothing loose about throat/chest to help vapors reach the nose/mouth
- repeat up to three times per 24 hours or as directed by doctor
- children under 2 years of age: ask a doctor

Other information

- store at room temperature

Inactive ingredients

cedarleaf oil, nutmeg oil, special petrolatum, spirits of turpentine, thymol

Questions?

Call 1-888-423-0139

ADVERSE REACTION

The active ingredients in Top Care Vaporizing Rub work when you inhale in the medicated vapors to relieve coughing due to colds. Top Care Vaporizing Rub also relieves monor muscle aches and pains.

*This product is not manufactured or distributed by Procter & Gamble, distributor of Vicks®VapoRub®

DISTRIBUTED BY: TOPCO ASSOCIATES LLC

ELK GROVE VILLAGE, IL 60077

TOPCO VIJA0521

QUESTIONS? 1-888-423-0139

topcare@topco.com www.topcarebrand.com

Scan here for more information or call 1-888-423-0139

Qualiy Guaranteed

This TopCare®product is laboratory tested to guarantee its highest quality. Your totla satisfaction is guaranteed.

Principal display panel

TopCare®

health

COMPARE TO VICKS®VAPORUB®ACTIVE INGREDIENTS*

Vaporizing

Rub

COUGH SUPPRESSANT

TOPICAL ANALGESIC

- Relives Coughing Due to Colds
- Relieves Minor Muscle Aches and Pains
- Soothing Ointment

NET WT 3.53 OZ (100 g)